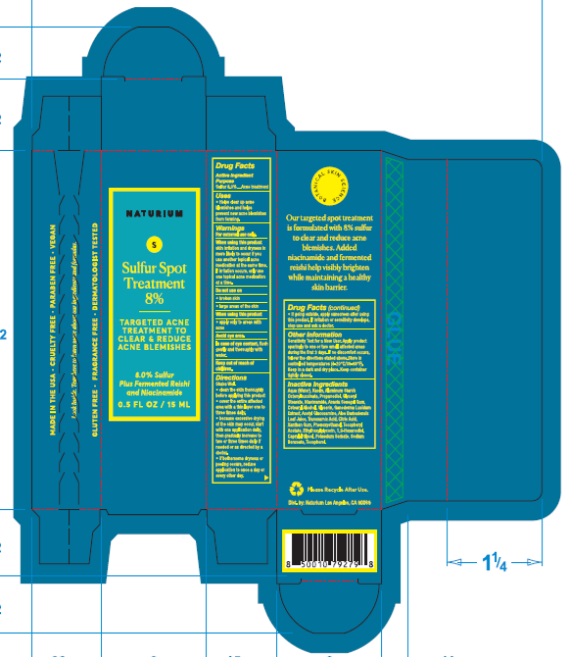 DRUG LABEL: Naturium Sulfur Spot Treatment 8%
NDC: 76354-120 | Form: LIQUID
Manufacturer: e.l.f. Cosmetics, Inc
Category: otc | Type: HUMAN OTC DRUG LABEL
Date: 20251114

ACTIVE INGREDIENTS: SULFUR 80 mg/1 mL
INACTIVE INGREDIENTS: WATER; KAOLIN; ALOE VERA LEAF; XANTHAN GUM; PHENOXYETHANOL; ETHYLHEXYLGLYCERIN; PROPANEDIOL; NIACINAMIDE; CETOSTEARYL ALCOHOL; ANHYDROUS CITRIC ACID; ALUMINUM STARCH OCTENYLSUCCINATE; CAPRYLYL GLYCOL; POTASSIUM SORBATE; SODIUM BENZOATE; .ALPHA.-TOCOPHEROL ACETATE; 1,2-HEXANEDIOL; TOCOPHEROL; ACACIA; GLYCERYL MONOSTEARATE; GLYCERIN; GANODERMA LUCIDUM WHOLE; N-ACETYLGLUCOSAMINE; TRANEXAMIC ACID

Naturium Sulfur Spot Treatment 8%

Active Ingredient

Sulfur 8.0%

Purpose

Acne treatment

Uses

- Helps clear up acne blemishes and helps prevent new acne blemishes from forming.

Warnings

For external use only.

When using this product

- skin irritation and dryness is more likely to occur if you use another topical acne medication at the same time. If irritation occurs, only use one topical acne medication at a time.
- apply only to areas with acne
- Avoid eye area. In case of eye contact, flush gently and thoroughly with water.

Do not use on

- broken skin
- large areas of the skin

Directions

Shake Well

- clean the skin thoroughly before applying this product
- cover the entire affected area with a thin layer one to three times daily
- because excessive drying of the skin may occur, start with one application daily, then gradually increase to two or three times daily if needed or as directed by a doctor
- if bothersome dryness or peeling occurs, reduce application to once a day or every other day.
- if going outside, apply sunscreen after using this product. If irritation or sensitivity develops, stop use and ask a doctor.

Other Information

Sensitivity Test for a New User. Apply product sparingly to one or two small affected areas during the first 3 days. If no discomfort occurs, follow the directions stated above.Store in controlled temperatures (4-20°C/39-68°F). Keep in a dark and dry place. Keep container tightly closed.

Inactive Ingredients

Aqua (Water), Kaolin, Aluminum Starch Octenylsuccinate, Propanediol, Glyceryl Stearate, Niacinamide, Acacia Senegal Gum, Cetearyl Alcohol, Glycerin, Ganoderma Lucidum Extract, Acetyl Glucosamine, Aloe Barbadensis Leaf Juice, Tranexamic Acid, Citric Acid, Xanthan Gum, Phenoxyethanol, Tocopheryl Acetate, Ethylhexylglycerin, 1,2-Hexanediol, Caprylyl Glycol, Potassium Sorbate, Sodium Benzoate, Tocopherol.